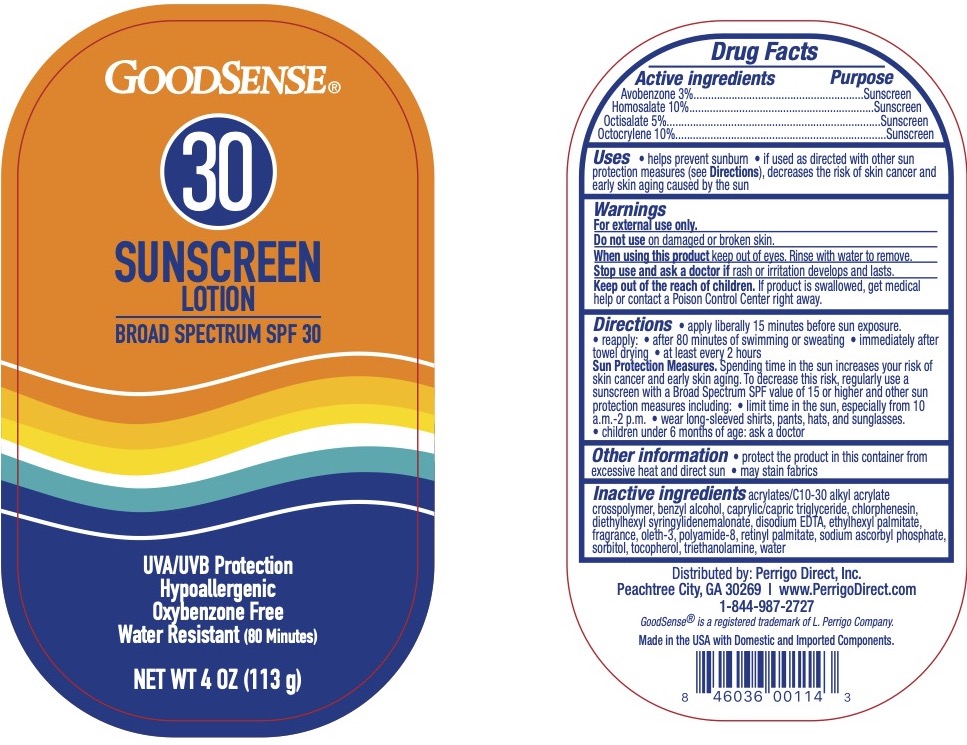 DRUG LABEL: GoodSense SPF 30 Sunscreen
NDC: 50804-221 | Form: LOTION
Manufacturer: Geiss, Destin, & Dunn, Inc.
Category: otc | Type: HUMAN OTC DRUG LABEL
Date: 20251102

ACTIVE INGREDIENTS: OCTISALATE 5 g/100 mL; AVOBENZONE 3 g/100 mL; OCTOCRYLENE 10 g/100 mL; HOMOSALATE 10 g/100 mL
INACTIVE INGREDIENTS: TROLAMINE; EDETATE DISODIUM; ACRYLATE/ISOBUTYL METHACRYLATE/N-TERT-OCTYLACRYLAMIDE COPOLYMER (75000 MW); MEDIUM-CHAIN TRIGLYCERIDES; DIETHYLHEXYL SYRINGYLIDENEMALONATE; TOCOPHEROL; BENZYL ALCOHOL; ETHYLHEXYL PALMITATE; OLETH-3; POLYAMIDE-8 (4500 MW); VITAMIN A PALMITATE; SODIUM ASCORBYL PHOSPHATE; SORBITOL; CHLORPHENESIN; WATER

GoodSense SPF 30 Sunscreen

Active Ingredients

Avobenzone 3%, Homosalate 10%, Octisalate 5%, Octocrylene 10%

Purpose

Sunscreen

Uses

Helps prevent sunburn

Warnings

For external use only.

Do not use on damaged or broken skin. When using this product keep out of eyes. Rinse eyes with water to remove.

Stop use and ask a doctor if rash occurs.

Keep Out of Reach of Children.

If swallowed, get medical help or contact a Poison Control Center right away.

Directions

Apply liberally 15 minutes before sun exposure. Reapply:

- after 80 minutes of swimming or sweating
- immediately after towel drying
- at least every 2 hours

Sun protection measures: spending time n the sun increases your risk of skin cancer and early skin aging. To decrease risk, regularly use a sunscreen with broad spectrum SPF of 15 or higher and other sun protection measure including:

- limit time in the sun, especially from 10 am to 2 pm
- wear long-sleeved shirts, pants, hats, and sunglasses.
- Children under 6 months: ask a doctor.

Inactive Ingredients

Acrylates/Octylacrylamide Copolymer, Benzyl Alcohol, Caprylic/Capric Triglyceride, Chlorphenesin, Diethylhexyl Syringylidenemalonate, Disodium EDTA, Ethylhexyl Palmitate, Fragrance, Oleth-3, Polyamide-8, Sodium Ascorbyl Phosphate, Sorbitol, Tocopherol, Triethanolamine, Water.